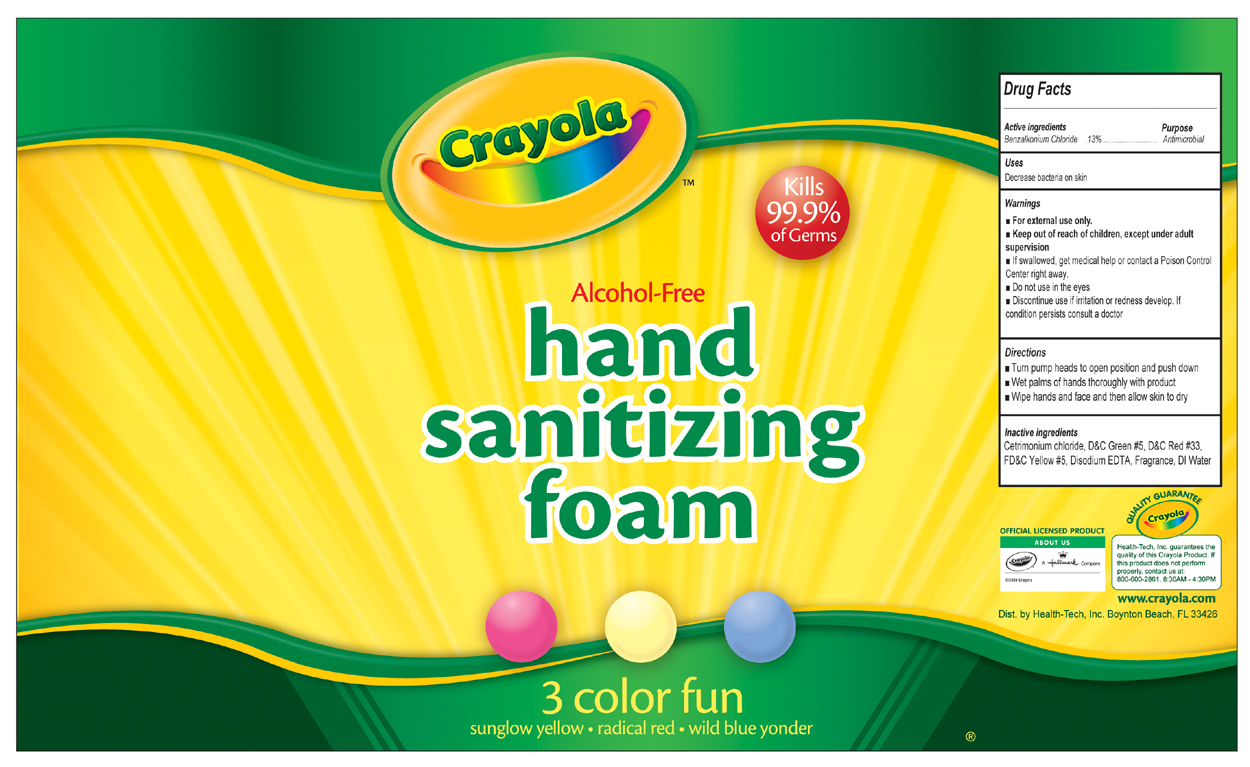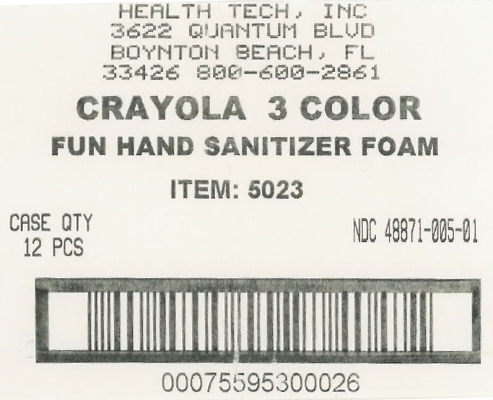 DRUG LABEL: Crayola Hand Sanitizing Foam
NDC: 48871-005 | Form: SPRAY
Manufacturer: Health-Tech, Inc.
Category: otc | Type: HUMAN OTC DRUG LABEL
Date: 20100525

ACTIVE INGREDIENTS: benzalkonium chloride .0013 mL/1 mL
INACTIVE INGREDIENTS: cetrimonium chloride; edetate disodium; water

Drug Facts

Active Ingredient

Benzalkonium Chloride 0.13%

Purpose

Antimicrobial

Uses

Decrease bacteria on skin

Warnings

- For external use only
- keep out of reach of children except under adult supervision
- If swallowed, get medical help or contact a Poison Control Center right away.
- Do not use in eyes.
- Discontinue use if irritation or redness develop. If condition persists consult a doctor.

Directions

- Turn pump heads to open position and push down
- Wet palms of hands thoroughly with product
- Wipe hands and face and then allow skin to dry

Inactive Ingredients

Cetrimonium chloride, D and C Green 5, D and C Red 33, FD and C Yellow 5, Disodium EDTA, DI water, Fragrance

Crayola Foam triple fun label

MM22

Crayola Foam triple fun shipper label

MM23